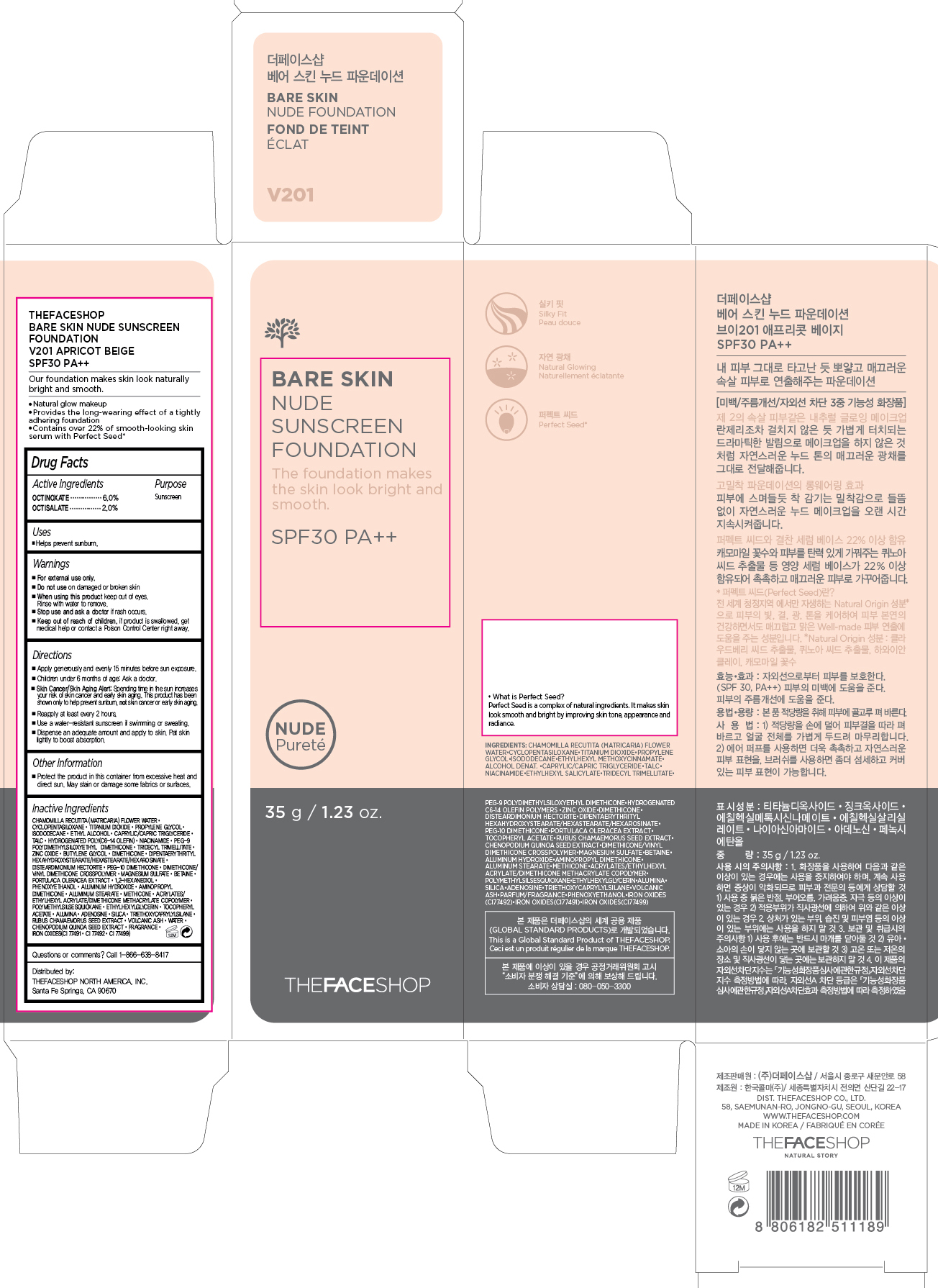 DRUG LABEL: BARE SKIN
NDC: 51523-366 | Form: CREAM
Manufacturer: THEFACESHOP CO., LTD.
Category: otc | Type: HUMAN OTC DRUG LABEL
Date: 20150929

ACTIVE INGREDIENTS: OCTINOXATE 2.1 g/35 g; OCTISALATE 0.7 g/35 g
INACTIVE INGREDIENTS: WATER

BARE SKIN NUDE SUNSCREEN FOUNDATION SPF30 PA++ 34200366

Active Ingredients

Octinoxate 6.0 %
Octisalate 2.0 %

Purpose

Sunscreen
Sunscreen

Uses:

Helps prevent sunburn.

Warnings

For external use only.

Do not use on damaged or broken skin

When using this product keep out of eyes. Rinse with water to remove.

Stop use and ask a doctor if rash occurs.

Keep out of reach of children. If product is swallowed, get medical help or contact a Poison Control Center right away.

Directions

Apply generously and evenly 15 minutes before sun exposure.
Children under 6 months of age: Ask a doctor.
Skin Cancer/Skin Aging Alert: Spending time in the sun increases your risk of skin cancer and early skin aging. This product has been shown only to help prevent sunburn, not skin cancer or early skin aging.
Reapply at least every 2 hours.
Use a water-resistant sunscreen if swimming or sweating.

Dispense an adequate amount and apply to skin. Pat skin lightly to boost absorption.

OTHER SAFETY INFORMATION

Protect the product in this container from excessive heat and direct sun.

May stain or damage some fabrics or surfaces.

Inactive Ingredients:

CHAMOMILLA RECUTITA (MATRICARIA) FLOWER WATER, CYCLOPENTASILOXANE, TITANIUM DIOXIDE, PROPYLENE GLYCOL, ISODODECANE, ETHYL ALCOHOL, CAPRYLIC/CAPRIC TRIGLYCERIDE, TALC, HYDROGENATED POLY(C6-14 OLEFIN), NIACINAMIDE, PEG-9 POLYDIMETHYLSILOXYETHYL DIMETHICONE, TRIDECYL TRIMELLITATE, ZINC OXIDE, BUTYLENE GLYCOL, DIMETHICONE, DIPENTAERYTHRITYL HEXAHYDROXYSTEARATE/HEXASTEARATE/HEXAROSINATE, DISTEARDIMONIUM HECTORITE, PEG-10 DIMETHICONE, DIMETHICONE/VINYL DIMETHICONE CROSSPOLYMER, MAGNESIUM SULFATE, BETAINE, PORTULACA OLERACEA EXTRACT, 1,2-HEXANEDIOL, PHENOXYETHANOL, ALUMINUM HYDROXIDE, AMINOPROPYL DIMETHICONE, ALUMINUM STEARATE, METHICONE, ACRYLATES/ETHYLHEXYL ACRYLATE/DIMETHICONE METHACRYLATE COPOLYMER, POLYMETHYLSILSESQUIOXANE, ETHYLHEXYLGLYCERIN, TOCOPHERYL ACETATE, ALUMINA, ADENOSINE, SILICA, TRIETHOXYCAPRYLYLSILANE, RUBUS CHAMAEMORUS SEED EXTRACT, VOLCANIC ASH, WATER, CHENOPODIUM QUINOA SEED EXTRACT, FRAGRANCE, IRON OXIDES(CI 77491, CI 77492, CI 77499)

Questions or comments? Call 1-866-638-8417

Distributed by:

THEFACESHOP NORTH AMERICA, INC.

Santa Fe Springs, CA 90670

PACKAGE LABEL

THEFACESHOP

BARE SKIN NUDE SUNSCREEN

FOUNDATION

V201 APRICOT BEIGE

SPF30 PA++

Our foundation makes skin look naturally bright and smooth.

•Natural glow makeup

•Provides the long-wearing eect of a tightly adhering foundation

•Contains over 22% of smooth-looking skin serum with Perfect Seed*